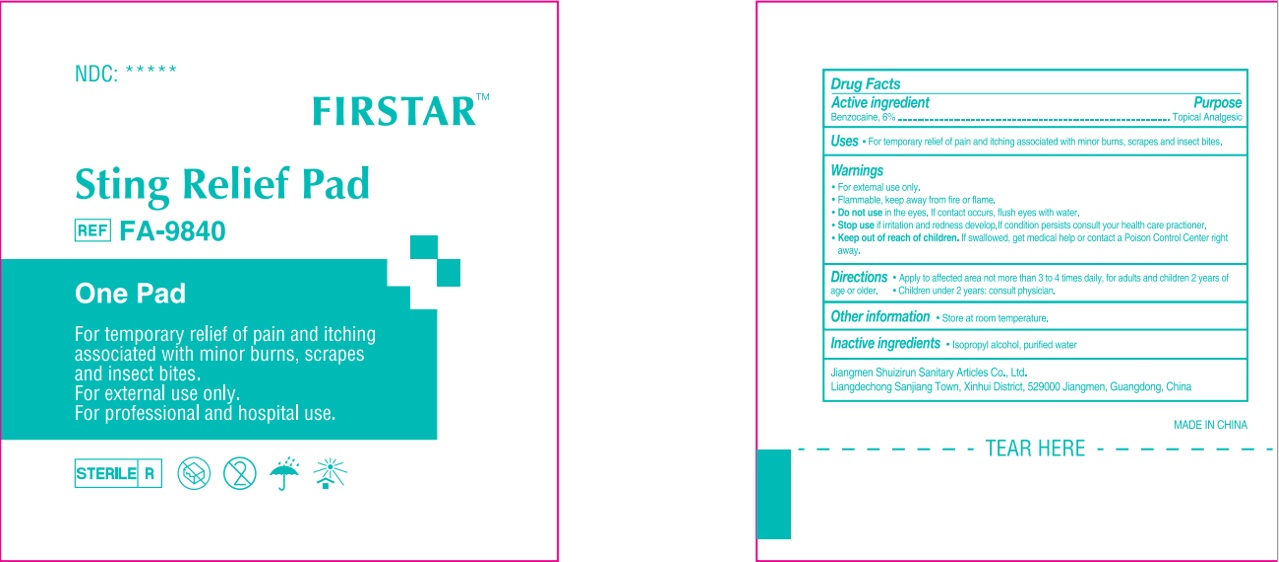 DRUG LABEL: FIRSTAR Sting Relief  Pad
NDC: 71734-113 | Form: CLOTH
Manufacturer: JIANGMEN SHUIZIRUN SANITARY ARTICLES CO., LTD.
Category: otc | Type: HUMAN OTC DRUG LABEL
Date: 20210706

ACTIVE INGREDIENTS: Benzocaine 6 g/100 g
INACTIVE INGREDIENTS: Isopropyl Alcohol; water

DRUG FACTS

Active Ingredient

Benzocaine ..........................6%

Purpose

Topical Analgesic

Uses:

For temporary relief of pain and itching associated with minor burns ,scrapes and insect bites.

Warnings

For external use only.

Flammable .Keep away from fire or flame.

Do not use in the eyes. If contact occurs ,flush eyes with water.

Keep out of reach of children.

If swallowed, get medical help or contact a Poison Control Center right away.

Directions

Apply to affected area not more than 3 to 4 times daily, for adults and children 2 years of age or older. Children under 2 years : consult physician.

Other Information: Store at room temperature.

INACTIVE INGREDIENT

Isopropyl Alcohol, Purified Water